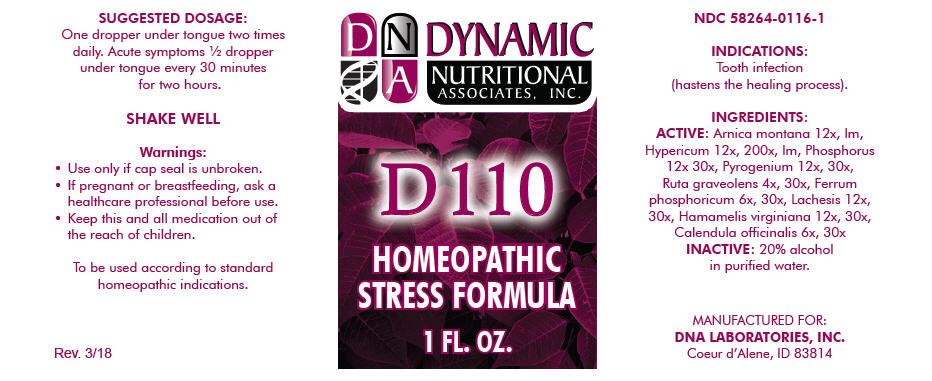 DRUG LABEL: D-110
NDC: 58264-0116 | Form: SOLUTION
Manufacturer: DNA Labs, Inc.
Category: homeopathic | Type: HUMAN OTC DRUG LABEL
Date: 20250113

ACTIVE INGREDIENTS: ARNICA MONTANA 12 [hp_X]/1 mL; HYPERICUM PERFORATUM 12 [hp_X]/1 mL; PHOSPHORUS 12 [hp_X]/1 mL; RANCID BEEF 12 [hp_X]/1 mL; RUTA GRAVEOLENS FLOWERING TOP 4 [hp_X]/1 mL; FERROSOFERRIC PHOSPHATE 6 [hp_X]/1 mL; LACHESIS MUTA VENOM 12 [hp_X]/1 mL; HAMAMELIS VIRGINIANA ROOT BARK/STEM BARK 12 [hp_X]/1 mL; CALENDULA OFFICINALIS FLOWERING TOP 6 [hp_X]/1 mL
INACTIVE INGREDIENTS: ALCOHOL; WATER

D-110

NDC 58264-0116-1

INDICATIONS

PURPOSE

Tooth infection (hastens the healing process).

INGREDIENTS

ACTIVE

Arnica montana 12x, lm, Hypericum 12x, 200x, lm, Phosphorus 12x 30x, Pyrogenium 12x, 30x, Ruta graveolens 4x, 30x, Ferrum phosphoricum 6x, 30x, Lachesis 12x, 30x, Hamamelis virginiana 12x, 30x, Calendula officinalis 6x, 30x

INACTIVE

20% alcohol in purified water.

SUGGESTED DOSAGE

One dropper under tongue two times daily. Acute symptoms ½ dropper under tongue every 30 minutes for two hours.

STORAGE AND HANDLING

SHAKE WELL

Warnings

- Use only if cap seal is unbroken.

PREGNANCY OR BREAST FEEDING

- If pregnant or breastfeeding, ask a healthcare professional before use.

KEEP OUT OF REACH OF CHILDREN

- Keep this and all medication out of the reach of children.

To be used according to standard homeopathic indications.

PRINCIPAL DISPLAY PANEL - 1 FL. OZ. Bottle Label

DYNAMIC
NUTRITIONAL
ASSOCIATES, INC.

D 110

HOMEOPATHIC
STRESS FORMULA

1 FL. OZ.